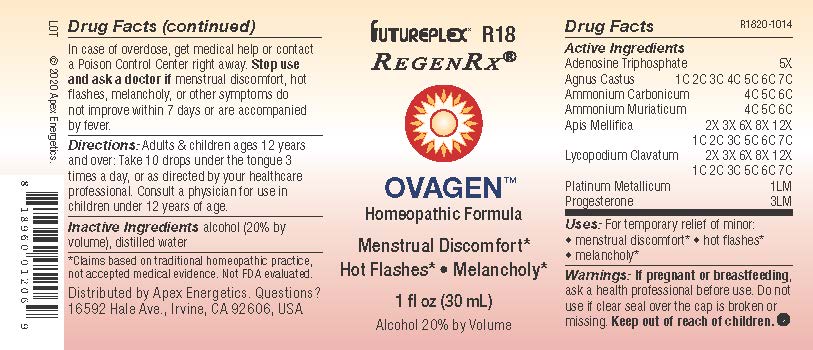 DRUG LABEL: R18
NDC: 63479-1818 | Form: SOLUTION/ DROPS
Manufacturer: Apex Energetics Inc.
Category: homeopathic | Type: HUMAN OTC DRUG LABEL
Date: 20240108

ACTIVE INGREDIENTS: ADENOSINE TRIPHOSPHATE 5 [hp_X]/1 mL; AMMONIUM CHLORIDE 6 [hp_C]/1 mL; PLATINUM 1 [hp_Q]/1 mL; PROGESTERONE 3 [hp_Q]/1 mL; APIS MELLIFERA 7 [hp_C]/1 mL; CHASTE TREE 7 [hp_C]/1 mL; AMMONIUM CARBONATE 6 [hp_C]/1 mL; LYCOPODIUM CLAVATUM SPORE 7 [hp_C]/1 mL
INACTIVE INGREDIENTS: ALCOHOL; WATER

R18

Active Ingredients
Adenosine Triphosphate | 5X
Agnus Castus | 1C 2C 3C 4C 5C 6C 7C
Ammonium Carbonicum | 4C 5C 6C
Ammonium Muriaticum | 4C 5C 6C
Apis Mellifica | 2X 3X 6X 8X 12X 1C 2C 3C 5C 6C 7C
Lycopodium Clavatum | 2X 3X 6X 8X 12X 1C 2C 3C 5C 6C 7C
Platinum Metallicum | 1LM
Progesterone | 3LM

INDICATIONS AND USAGE

Uses:

For temporary relief of minor:

menstrual discomfort*

hot flashes*

melancholy*

*Claims based on traditional homeopathic practice, not accepted medical evidence. Not FDA evaluated.

Warnings:

PREGNANCY OR BREAST FEEDING

If pregnant or breastfeeding, ask a health professional before use.

Do not use if clear seal over the cap is broken or missing.

Keep out of reach of children. In case of overdose, get medical help or contact a Poison Control Center right away.

Stop use and ask a doctor if menstrual discomfort, hot flashes, melancholy, or other symptoms do not improve within 7 days or are accompanied by fever.

Directions:

Adults & children ages 12 years and over: Take 10 drops under the tongue 3 times a day, or as directed by your healthcare professional. Consult a physician for use in children under 12 years of age.

Inactive Ingredients

alcohol (20% by volume), distilled water

Distributed by Apex Energetics. Questions?

16592 Hale Ave., Irvine, CA 92606, USA

PACKAGE LABEL

FUTUREPLEX® R18

REGENRX®

OVAGEN™

Homeopathic Formula

Menstrual Discomfort*

Hot Flashes* Melancholy*

1 fl oz (30 mL)

Alcohol 20% by Volume